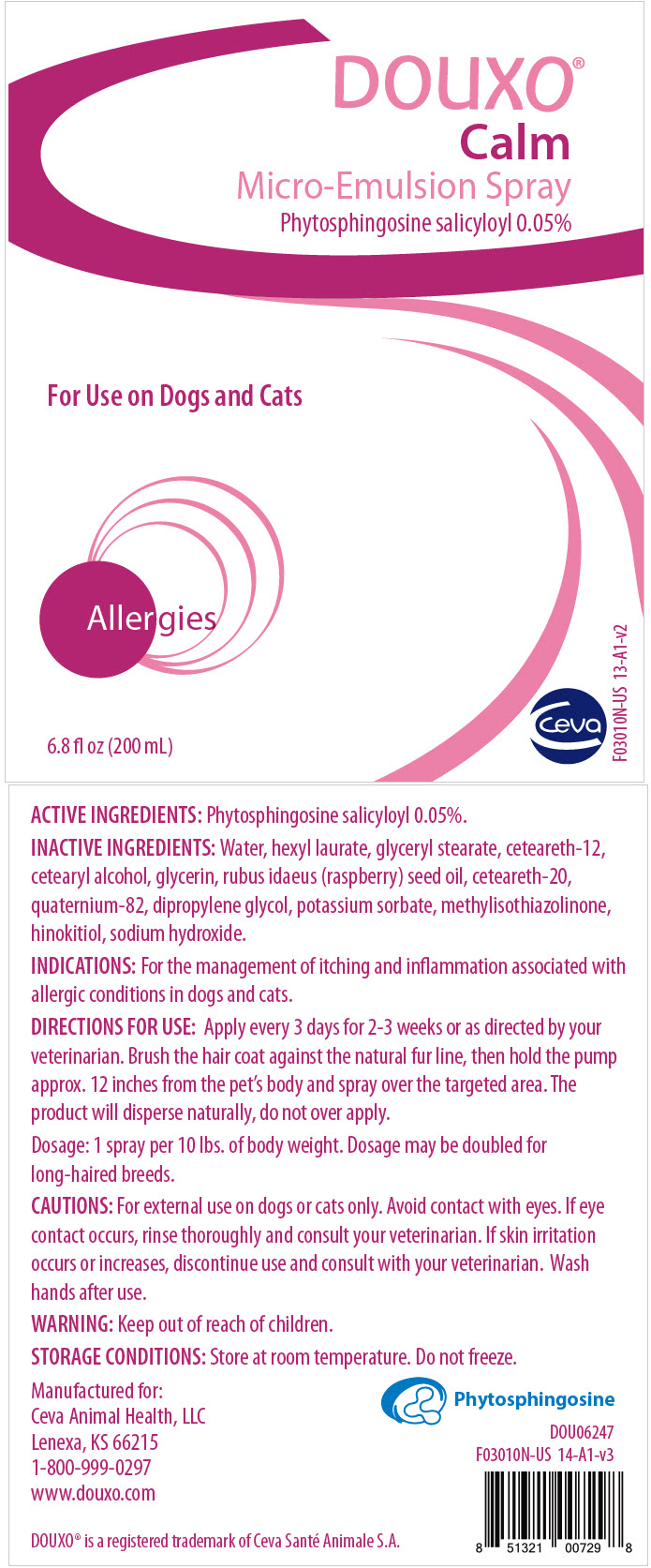 DRUG LABEL: DOUXO CALM
NDC: 13744-124 | Form: SPRAY
Manufacturer: Ceva Sante Animale
Category: animal | Type: OTC ANIMAL DRUG LABEL
Date: 20250905

ACTIVE INGREDIENTS: SALICYLOYL PHYTOSPHINGOSINE 0.5 mg/1 mL

DOUXO® CALM

DESCRIPTION

ACTIVE INGREDIENTS: Phytosphingosine salicyloyl 0.05%.

INACTIVE INGREDIENTS: Water, hexyl laurate, glyceryl stearate, ceteareth-12, cetearyl alcohol, glycerin, rubus idaeus (raspberry) seed oil, ceteareth-20, quaternium-82, dipropylene glycol, potassium sorbate, methylisothiazolinone, hinokitiol, sodium hydroxide.

VETERINARY INDICATIONS

INDICATIONS: For the management of itching and inflammation associated with allergic conditions in dogs and cats.

DOSAGE AND ADMINISTRATION

DIRECTIONS FOR USE: Apply every 3 days for 2-3 weeks or as directed by your veterinarian. Brush the hair coat against the natural fur line, then hold the pump approx. 12 inches from the pet's body and spray over the targeted area. The product will disperse naturally, do not over apply.

Dosage: 1 spray per 10 lbs. of body weight. Dosage may be doubled for long-haired breeds.

PRECAUTIONS

CAUTIONS: For external use on dogs or cats only. Avoid contact with eyes. If eye contact occurs, rinse thoroughly and consult your veterinarian. If skin irritation occurs or increases, discontinue use and consult with your veterinarian. Wash hands after use.

WARNINGS

WARNING: Keep out of reach of children.

STORAGE AND HANDLING

STORAGE CONDITIONS: Store at room temperature. Do not freeze.

Manufactured for:
Ceva Animal Health, LLC
Lenexa, KS 66215
1-800-999-0297
www.douxo.com

DOUXO® is a registered trademark of Ceva Santé Animale S.A.

Phytosphingosine

DOU06247

F03010N-US 14-A1-v3

PRINCIPAL DISPLAY PANEL - 200 mL Bottle Label

DOUXO®
Calm
Micro-Emulsion Spray
Phytosphingosine salicyloyl 0.05%

For Use on Dogs and Cats

Allergies

6.8 fl oz (200 mL)

ceva

F03010N-US 13-A1-v2